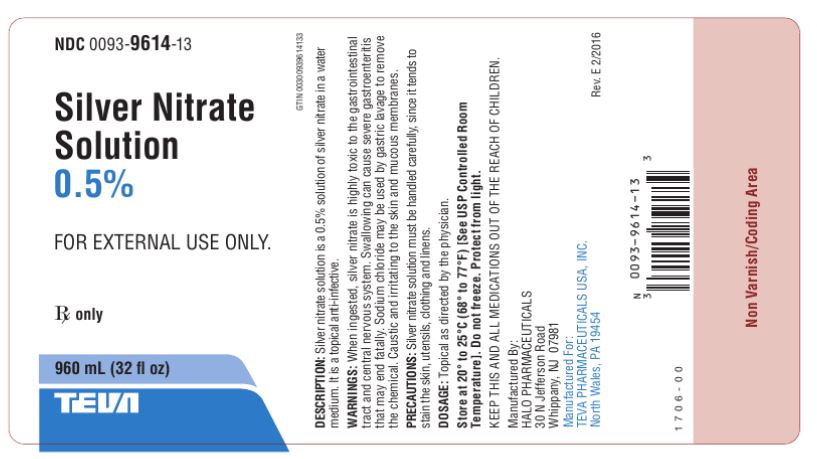 DRUG LABEL: Silver Nitrate
NDC: 0093-9614 | Form: SOLUTION
Manufacturer: Teva Pharmaceuticals USA, Inc.
Category: prescription | Type: HUMAN PRESCRIPTION DRUG LABEL
Date: 20160201

ACTIVE INGREDIENTS: SILVER NITRATE 0.005 g/1 mL
INACTIVE INGREDIENTS: WATER

Silver Nitrate Solution

Silver Nitrate Solution 0.5% 960 mL Label Text

NDC 0093-9614-13

Silver Nitrate

Solution

0.5%

FOR EXTERNAL USE ONLY.

Rx only

960 mL (32 fl oz)

TEVA

DESCRIPTION: Silver nitrate solution is a 0.5% solution of

silver nitrate in a water medium. It is a topical anti-infective.

WARNINGS: When ingested, silver nitrate is highly toxic to

the gastrointestinal tract and central nervous system.

Swallowing can cause severe gastroenteritis that may end

fatally. Sodium chloride may be used by gastric lavage to

remove the chemical. Caustic and irritating to the skin and

mucous membranes.

PRECAUTIONS: Silver nitrate solution must be handled carefully,
since it tends to stain the skin, utensils, clothing and linens.

DOSAGE: Topical as directed by the physician.

Store at 20° to 25°C (68° to 77°F) [See USP Controlled

Room Temperature]. Do not freeze. Protect from light.

KEEP THIS AND ALL MEDICATIONS OUT OF THE REACH

OF CHILDREN.

Manufactured By:

HALO PHARMACEUTICALS

30 N Jefferson Road

Whippany, NJ 07981

Manufactured For:

TEVA PHARMACEUTICALS USA, INC.

North Wales, PA 19454

333-32-101019 Rev. E 2/2016
102121 0786-01